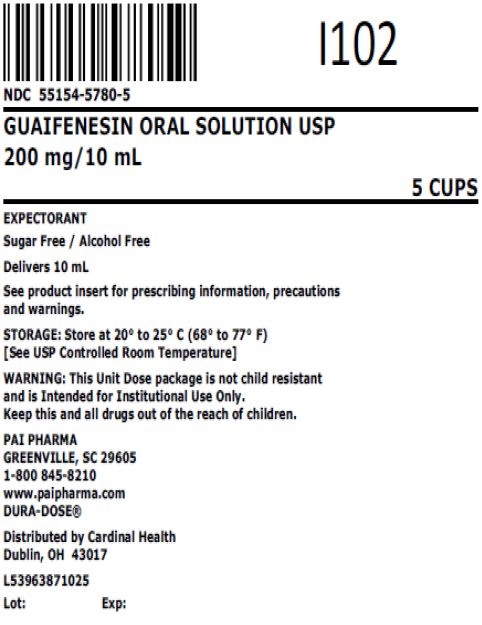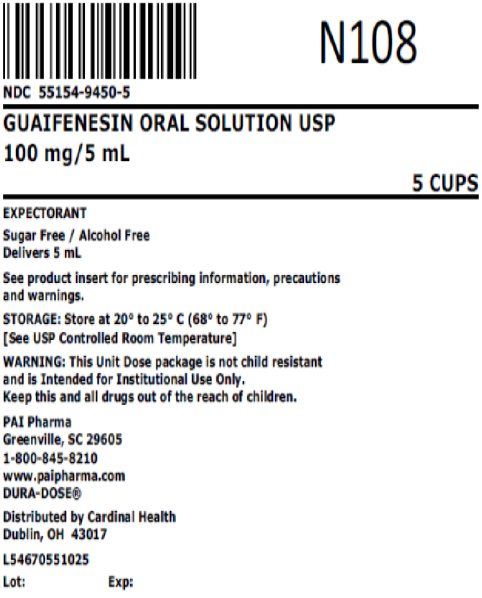 DRUG LABEL: GUAIFENESIN
NDC: 55154-9450 | Form: SOLUTION
Manufacturer: Cardinal Health 107, LLC
Category: otc | Type: HUMAN OTC DRUG LABEL
Date: 20251107

ACTIVE INGREDIENTS: GUAIFENESIN 100 mg/5 mL
INACTIVE INGREDIENTS: ACESULFAME POTASSIUM; ANHYDROUS CITRIC ACID; FD&C GREEN NO. 3; FD&C RED NO. 40; HYDROXYETHYL CELLULOSE (140 MPA.S AT 5%); WATER; SODIUM BENZOATE; SODIUM CITRATE, UNSPECIFIED FORM

GUAIFENESIN

PURPOSE

Expectorant
SUGAR FREE / ALCOHOL FREE

DESCRIPTION

Each 5 mL (1 teaspoonful) contains:
Guaifenesin 100 mg

Inactive Ingredients

Acesulfame K, citric acid, FD&C Green No. 3, FD&C Red No. 40, flavoring, hydroxyethylcellulose, purified water, sodium benzoate and sodium citrate.

Sodium Content: 4 mg/5 mL

USES

Helps loosen phlegm (mucus) and thin bronchial secretions to make coughs more productive.

WARNINGS

Ask a doctor before use if you have

- cough that occurs with too much phlegm (mucus)
- cough that lasts or is chronic such as occurs with smoking, asthma, chronic bronchitis, or emphysema

Stop use and ask a doctor if

- cough lasts more than 7 days, comes back, or is accompanied by fever, rash, or persistent headache. These could be signs of a serious condition.
- you are hypersensitive to any of the ingredients.

PREGNANCY OR BREAST FEEDING

If pregnant or breast-feeding, ask a health professional before use.

Keep out of reach of children. In case of overdose, get medical help or contact a Poison Control Center right away.

Professional Note

Guaifenesin has been shown to produce a color interference with certain clinical laboratory determinations of 5-hydroxyindoleacetic acid (5-HIAA) and vanillylmandelic acid (VMA).

DIRECTIONS

Follow dosage below or use as directed by a physician.

- do not take more than 6 doses in any 24-hour period.

age | dose
adults and children 12 years and over | 10 to 20 mL (2 to 4 teaspoonfuls) every 4 hours
children 6 years to under 12 years | 5 to 10 mL (1 to 2 teaspoonfuls) every 4 hours
children 2 to under 6 years of age | 2.5 to 5 mL (½ to 1 teaspoonful) every 4 hours
children under 2 years of age | consult a physician

Guaifenesin Oral Solution USP is a red, raspberry flavored solution supplied in the following oral dosage forms:

Overbagged with 5 x 5 mL unit dose cups in each bag, NDC 55154-9450-5

Overbagged with 5 x 10 mL unit dose cups in each bag, NDC 55154-5780-5

WARNING: These Unit Dose packages are not child resistant and are Intended for Institutional Use Only. Keep this and all drugs out of the reach of children.

Distributed By:

Cardinal Health

Dublin, OH 43017

L54670551025

L53963871025

STORAGE

Keep tightly closed. Store at controlled room temperature, 20°-25°C (68°-77°F). [See USP] Protect from light.

Principal Display Panel

NDC 55154-9450-5

GUAIFENESIN ORAL SOLUTION USP

100 mg/5mL

5 CUPS

Principal Display Panel

NDC 55154-5780-5

GUAIFENESIN ORAL SOLUTION USP

200 mg/10 mL

5 CUPS